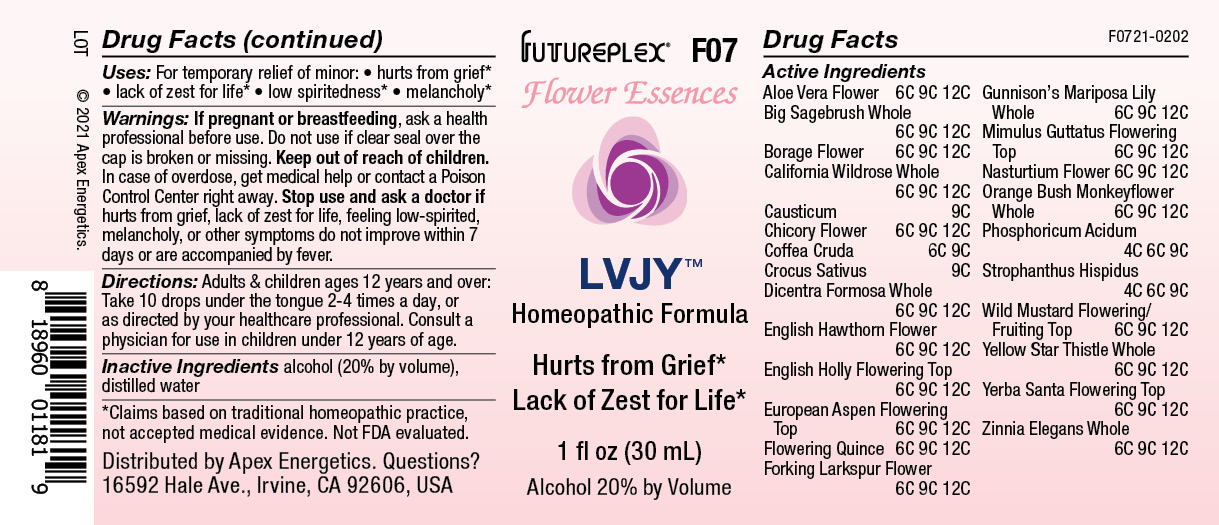 DRUG LABEL: F07
NDC: 63479-0607 | Form: SOLUTION/ DROPS
Manufacturer: Apex Energetics Inc.
Category: homeopathic | Type: HUMAN OTC DRUG LABEL
Date: 20240108

ACTIVE INGREDIENTS: CAUSTICUM 9 [hp_C]/1 mL; SAFFRON 9 [hp_C]/1 mL; CONSOLIDA REGALIS FLOWER 12 [hp_C]/1 mL; MIMULUS GUTTATUS FLOWERING TOP 12 [hp_C]/1 mL; TROPAEOLUM MAJUS FLOWER 12 [hp_C]/1 mL; PHOSPHORIC ACID 9 [hp_C]/1 mL; CENTAUREA SOLSTITIALIS WHOLE 12 [hp_C]/1 mL; ERIODICTYON CALIFORNICUM FLOWERING TOP 12 [hp_C]/1 mL; CRATAEGUS MONOGYNA FLOWER 12 [hp_C]/1 mL; POPULUS TREMULA FLOWERING TOP 12 [hp_C]/1 mL; ARTEMISIA TRIDENTATA WHOLE 12 [hp_C]/1 mL; ALOE VERA FLOWER 12 [hp_C]/1 mL; CALOCHORTUS GUNNISONII WHOLE 12 [hp_C]/1 mL; ZINNIA ELEGANS WHOLE 12 [hp_C]/1 mL; ROSA CALIFORNICA WHOLE 12 [hp_C]/1 mL; DIPLACUS AURANTIACUS WHOLE 12 [hp_C]/1 mL; BORAGO OFFICINALIS FLOWER 12 [hp_C]/1 mL; ILEX AQUIFOLIUM FLOWERING TOP 12 [hp_C]/1 mL; CHAENOMELES LAGENARIA WHOLE 12 [hp_C]/1 mL; CICHORIUM INTYBUS FLOWER 12 [hp_C]/1 mL; ARABICA COFFEE BEAN 9 [hp_C]/1 mL; STROPHANTHUS HISPIDUS SEED 9 [hp_C]/1 mL; SINAPIS ARVENSIS FLOWERING/FRUITING TOP 12 [hp_C]/1 mL; DICENTRA FORMOSA WHOLE 12 [hp_C]/1 mL
INACTIVE INGREDIENTS: WATER; ALCOHOL

F07

Active Ingredients
Aloe Vera Flower | 6C 9C 12C
Big Sagebrush Whole | 6C 9C 12C
Borage Flower | 6C 9C 12C
California Wildrose Whole | 6C 9C 12C
Causticum | 9C
Chicory Flower | 6C 9C 12C
Coffea Cruda | 6C 9C
Crocus Sativus | 9C
Dicentra Formosa Whole | 6C 9C 12C
English Hawthron Flower | 6C 9C 12C
English Holly Flowering Top | 6C 9C 12C
European Aspen Flowering Top | 6C 9C 12C
Flowering Quince | 6C 9C 12C
Forking Larkspur Flower | 6C 9C 12C
Gunnison's Mariposa Lily Whole | 6C 9C 12C
Mimulus Guttatus Flowering Top | 6C 9C 12C
Nasturtium Flower | 6C 9C 12C
Orange Bush Monkeyflower Whole | 6C 9C 12C
Phosphoricum Acidum | 4C 6C 9C
Strophanthus Hispidus | 4C 6C 9C
Wild Mustard Flowering/Fruiting Top | 6C 9C 12C
Yellow Star-Thistle Whole | 6C 9C 12C
Yerba Santa Flowering Top | 6C 9C 12C
Zinnia Elegans Whole | 6C 9C 12C

INDICATIONS AND USAGE

Uses:

For temporary relief of minor:

hurts from grief*

lack of zest for life*

low spiritedness*

melancholy*

*Claims based on traditional homeopathic practice, not accepted medical evidence. Not FDA evaluated.

Warnings:

PREGNANCY OR BREAST FEEDING

If pregnant or breastfeeding, ask a health professional before use.

Do not use if clear seal over the cap is broken or missing.

Keep out of reach of children. In case of overdose, get medical help or contact a Poison Control Center right away.

Stop use and ask a doctor if hurts from grief, lack of zest for life, feeling low-spirited, melancholy, or other symptoms do not improve within 7 days or are accompanied by fever.

Directions:

Adults & children ages 12 years and over: Take 10 drops under the tongue 2-4 times a day, or as directed by your healthcare professional. Consult a physician for use in children under 12 years of age.

Inactive Ingredients

alcohol (20% by volume), distilled water

Distributed by Apex Energetics. Questions?

16592 Hale Ave., Irvine, CA 92606, USA

PACKAGE LABEL

FUTUREPLEX® F07

Flower Essences

LVJY™

Homeopathic Formula

Hurts from Grief*

Lack of Zest for Life*

1 fl oz (30 mL)

Alcohol 20% by Volume